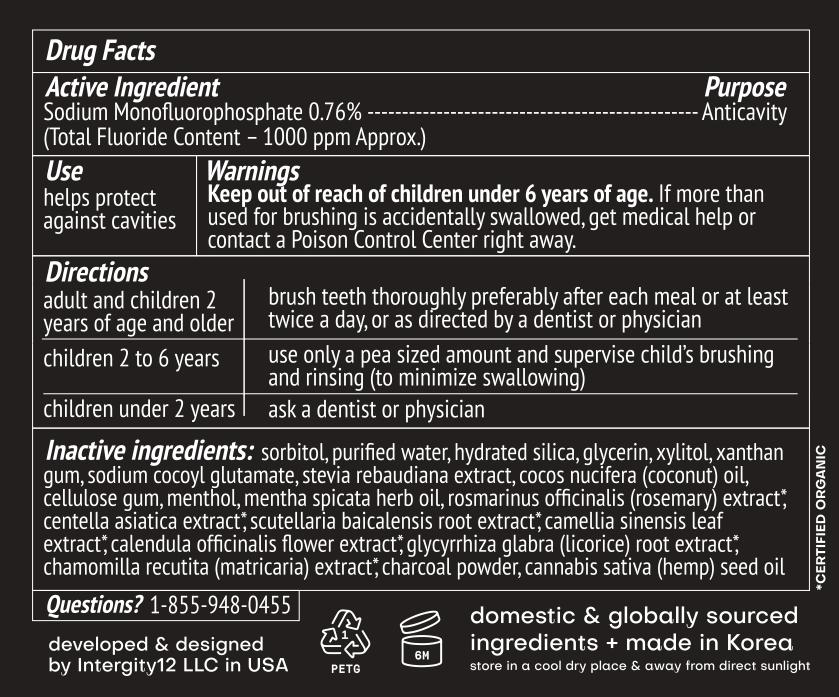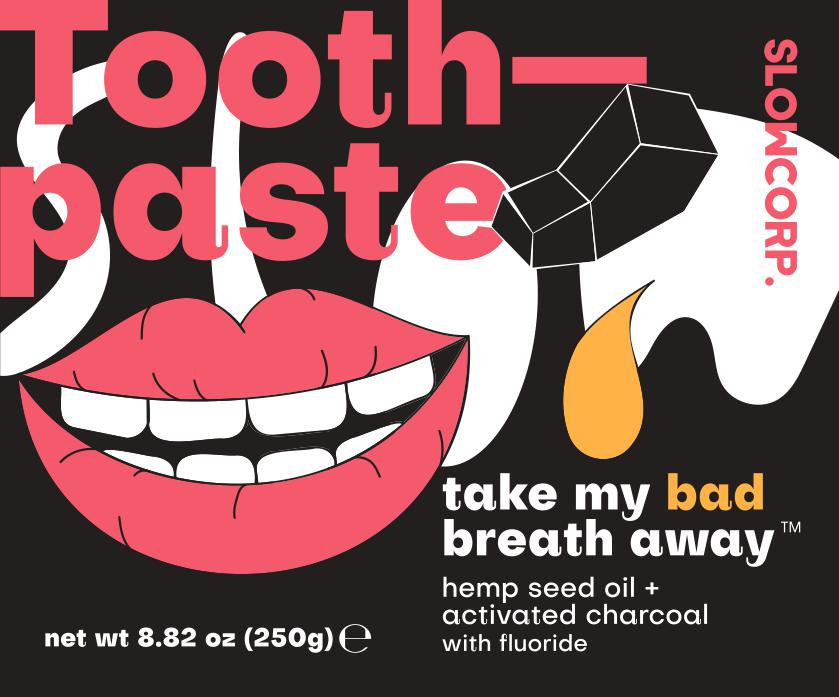 DRUG LABEL: Slow Corporation
NDC: 81111-100 | Form: PASTE
Manufacturer: Integrity12 Inc
Category: otc | Type: HUMAN OTC DRUG LABEL
Date: 20220113

ACTIVE INGREDIENTS: SODIUM MONOFLUOROPHOSPHATE 0.76 g/100 g
INACTIVE INGREDIENTS: WATER; STEVIA REBAUDIANA WHOLE; XANTHAN GUM; COCONUT OIL; XYLITOL; HYDRATED SILICA; GLYCERIN; CARBOXYMETHYLCELLULOSE SODIUM (0.7 CARBOXYMETHYL SUBSTITUTION PER SACCHARIDE; 1200 MPA.S AT 1%); SODIUM COCOYL GLUTAMATE; GREEN TEA LEAF; MENTHOL; SORBITOL; SPEARMINT OIL; ACTIVATED CHARCOAL; CANNABIS SATIVA SEED OIL; CENTELLA ASIATICA; SCUTELLARIA BAICALENSIS ROOT; CALENDULA OFFICINALIS FLOWER; GLYCYRRHIZA GLABRA; MATRICARIA RECUTITA

ACTIVE INGREDIENT

Sodium Monofluorophosphate 0.76%

Use

Helps protect against cavities

Keep out of reach of children under 6 years of age.

Directions:

Adult and children 2 years of age and older: brush teeth thoroughly preferably after each meal or at least twice a day, or as directed by a dentist or physician

Children 2 to 6 years: use only a pea sized amount and supervise child's brushing and rinsing (to minimize swallowing)

Children under 2 years: ask a dentist or physician.

WARNINGS

If more than used for brushing is accidentally swalloed, get medical help or contact a Poison Control Center right away.

INACTIVE INGREDIENT

Sorbitol, purified water, Hydrated silica, Glycerin, Xylitol, Xanthan gum, Sodium Cocoyl Glutamate, Stevia Rebaudiana Extract, Cocos Nucifera (Coconut) Oil, Cellulose Gum, Menthol, Mentha Spicata Herb Oil, Rosmarinus Offiicinalis (Rosemary) Extract, Centella Asiatica Extract, Scutellaria Baicalensis Root Extract, Camellia Sinensis Leaf Extract, Calendula Officinalis Flower Extract, Glycyrrhiza Glabra (Licorice) Root Extract, Chamomilla Recutita (Matricaria) Extract, Charcoal Powder, Cannabis Sativa (Hemp) Seed Oil

DOSAGE AND ADMINISTRATION

Paste pea size of toothpaste on the tooth brush

PACKAGE LABEL

250g; NDC 81111-100-01